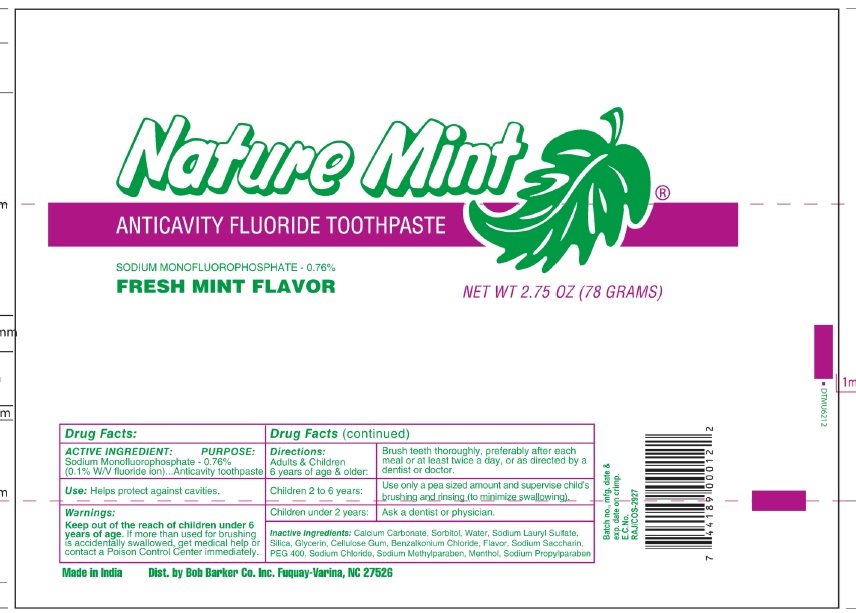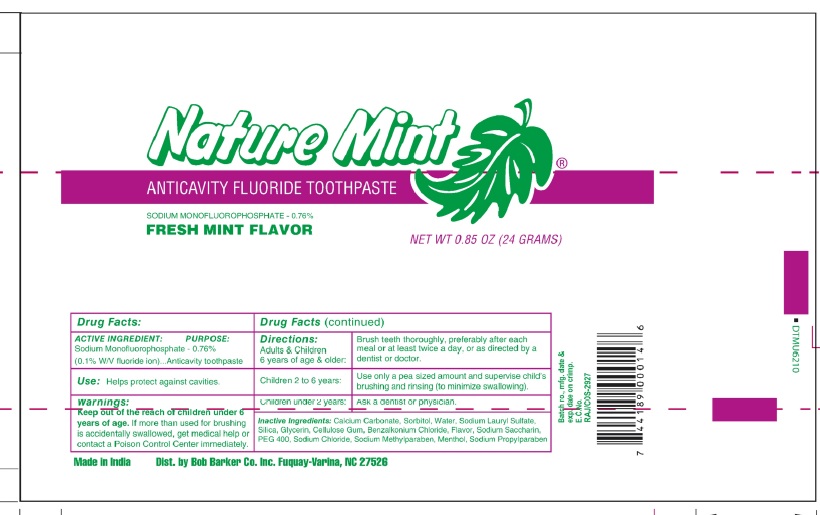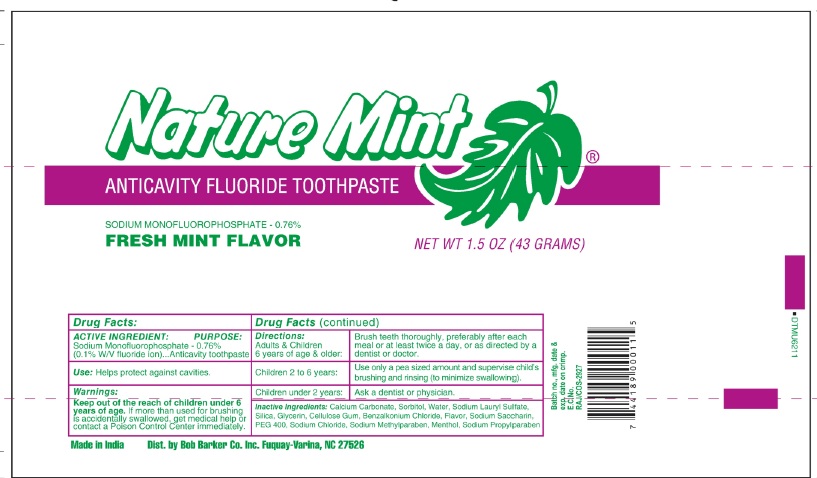 DRUG LABEL: Nature Mint Anti cavity Fluoride
NDC: 85891-009 | Form: PASTE
Manufacturer: SPARROW LIFE CARE PRIVATE LIMITED
Category: otc | Type: HUMAN OTC DRUG LABEL
Date: 20250825

ACTIVE INGREDIENTS: SODIUM MONOFLUOROPHOSPHATE 0.1 g/100 g
INACTIVE INGREDIENTS: CALCIUM CARBONATE; SORBITOL; WATER; SODIUM LAURYL SULFATE; SILICA; GLYCERIN; CARBOXYMETHYLCELLULOSE; BENZALKONIUM CHLORIDE; SODIUM SACCHARIN; POLYETHYLENE GLYCOL 400; SODIUM CHLORIDE; METHYLPARABEN SODIUM; MENTHOL; PROPYLPARABEN SODIUM

Active Ingredient

Sodium Monofluorophophate 0.76 % (0.1 % W/V Fluoride Ion)

Purpose

Anticavity Toothpaste

Uses

• Help Protect against cavities

Warnings

• Keep out of the reach of children under 6 years of age. If more than used for brushing is accidentally swallowed. Get medical help or contact a poison control center immediately

Directions

Adults & children 6 years of age & older: | Brush teeth thoroughly, Preferably after each meal of at least twice a day, or as directed by a dentist or doctor
Children 2 to 6 years | Use only pea sized amount and supervise child’s brushing and rinsing (to minimize swallowing).
Children under 2 years | Ask a dentist or physician

Inactive ingredients

Calcium carbonate, Sorbitol, Water, Sodium lauryl Sulfate, Silica, Glycerin, Cellulose Gum, Benzalkonium Chloride, Flavor, Sodium Saccharin, PEG 400, Sodium Chloride, Sodium Methyl paraben, Menthol, Sodium Propyl paraben